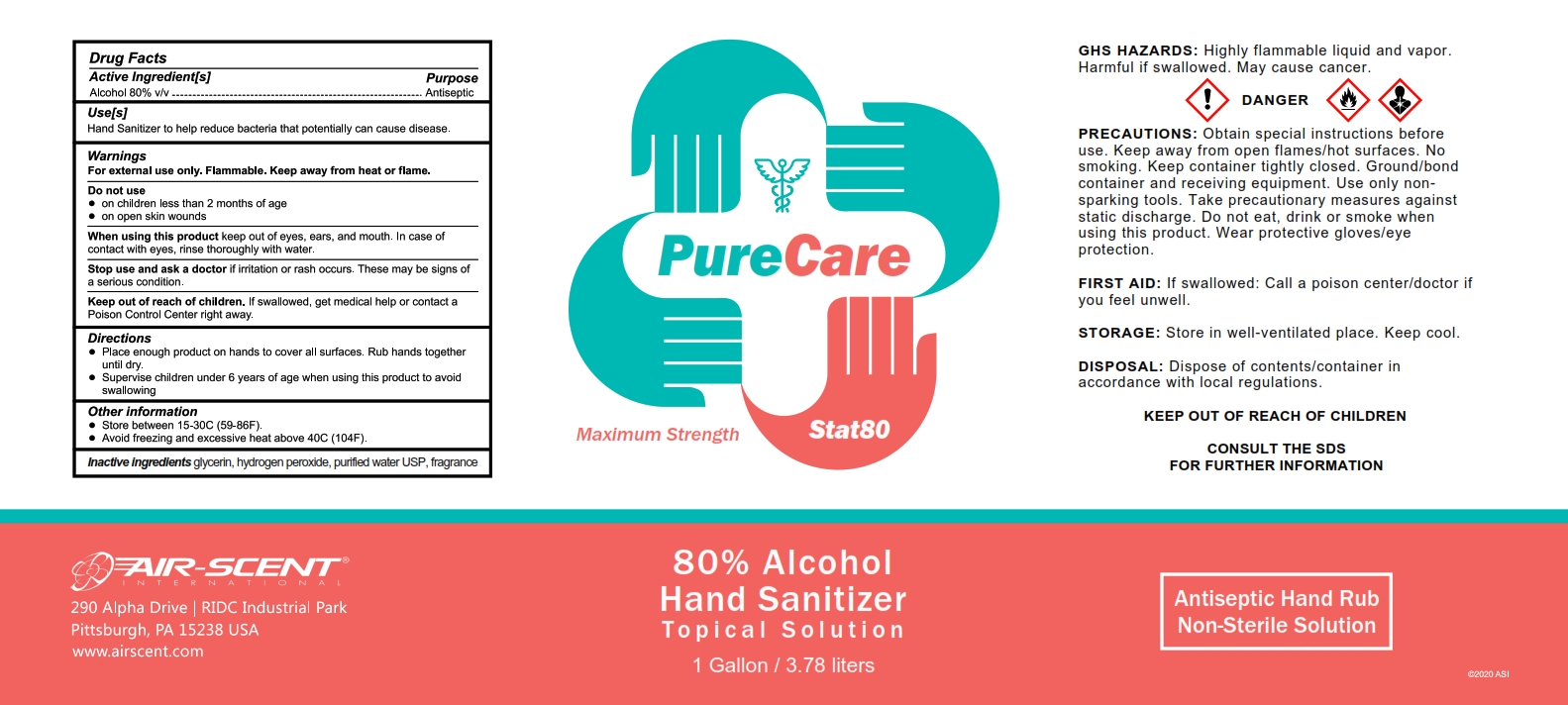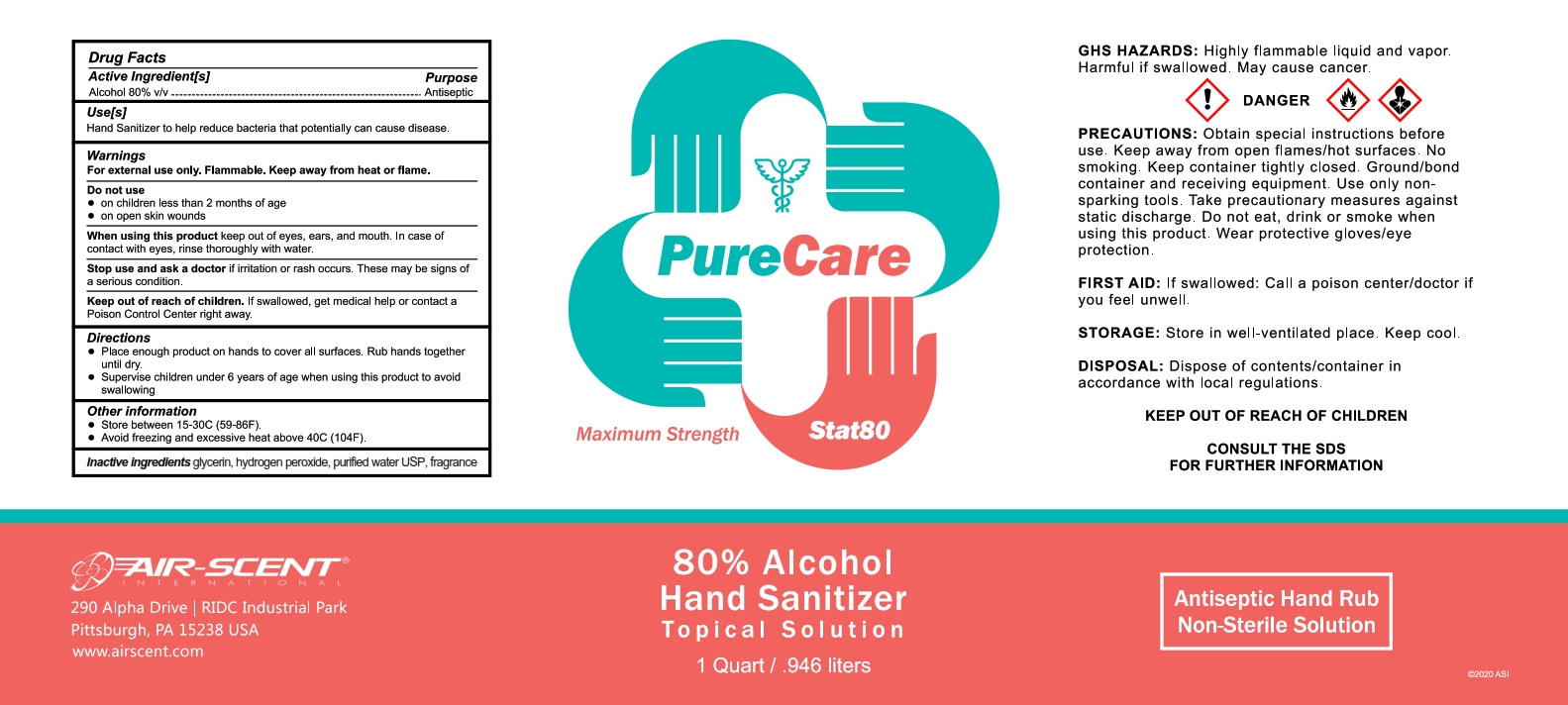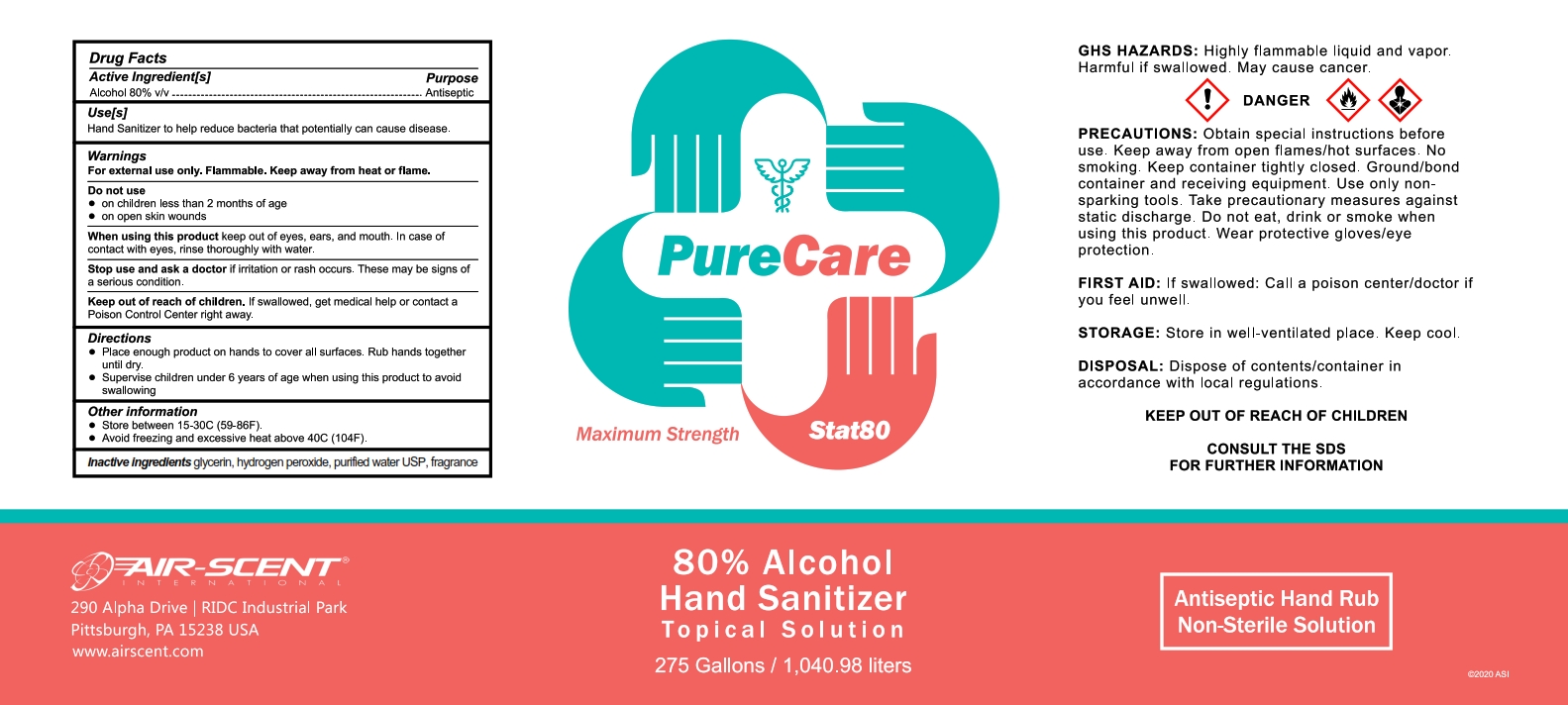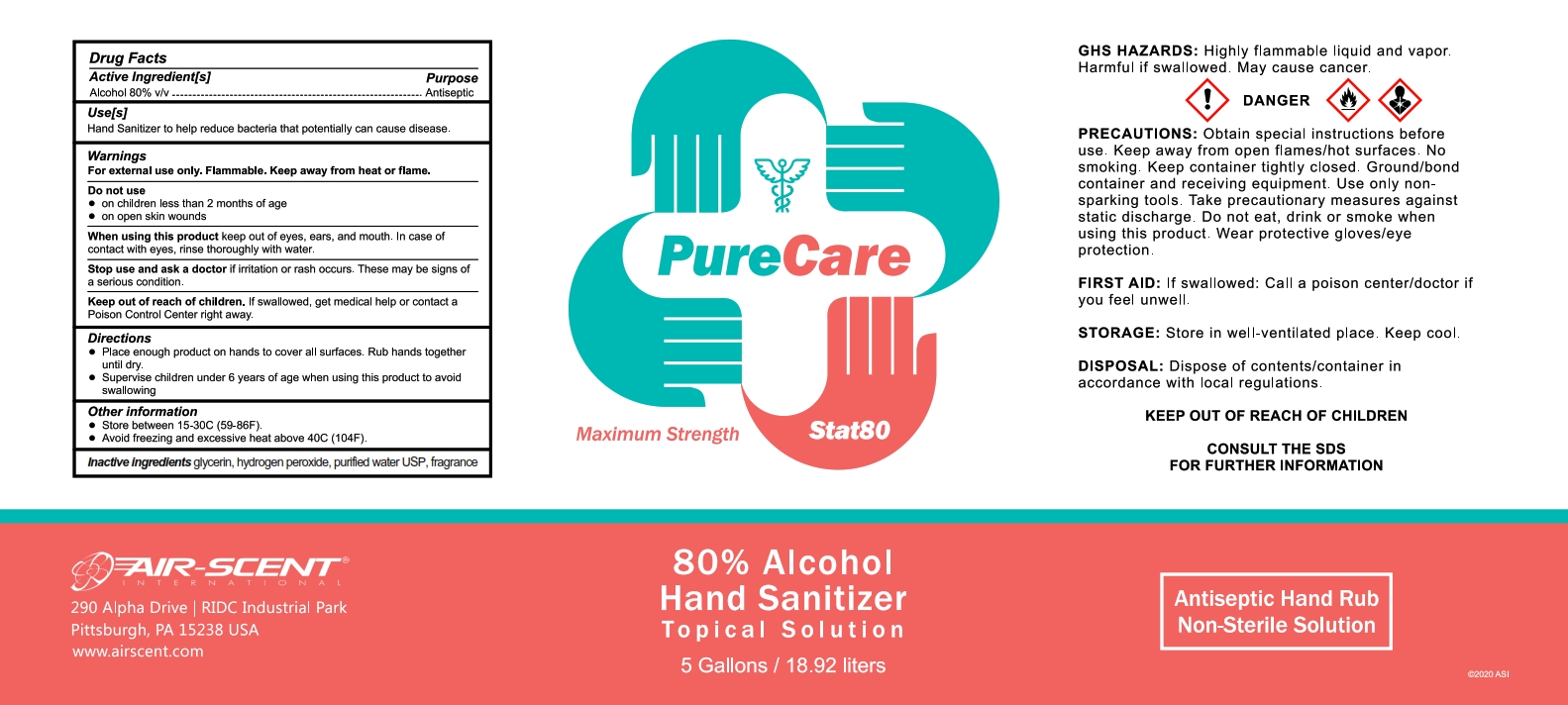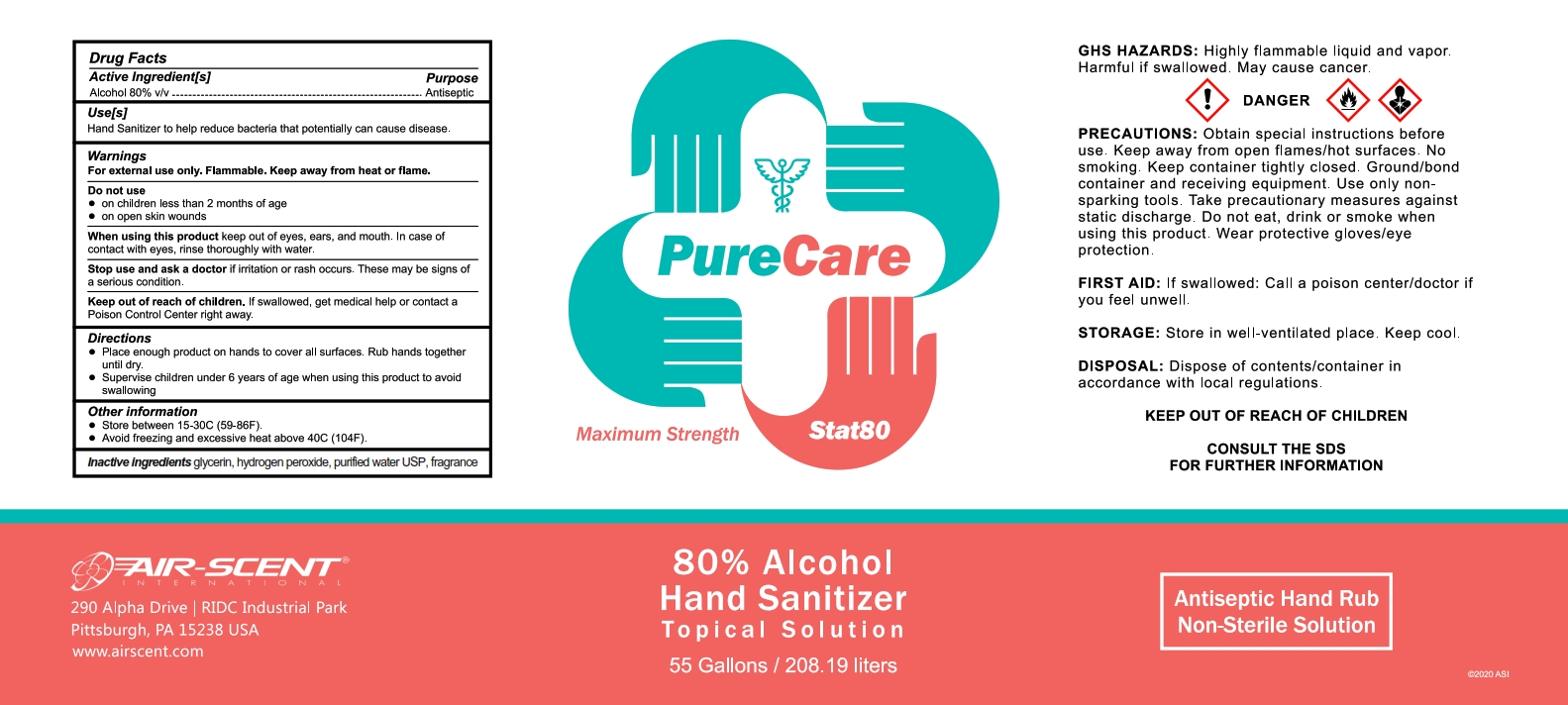 DRUG LABEL: Hand Sanitizer
NDC: 75009-680 | Form: LIQUID
Manufacturer: Alpha Aromatics
Category: otc | Type: HUMAN OTC DRUG LABEL
Date: 20220121

ACTIVE INGREDIENTS: ALCOHOL 80 mL/100 mL
INACTIVE INGREDIENTS: DIHYDROMYRCENOL 0.02 mL/100 mL; 4-TERT-BUTYLCYCLOHEXYL ACETATE 0.01 mL/100 mL; .ALPHA.-HEXYLCINNAMALDEHYDE 0.005 mL/100 mL; LINALOOL, (+/-)- 0.05 mL/100 mL; BUTYLPHENYL METHYLPROPIONAL 0.02 mL/100 mL; GLYCERIN 1.45 mL/100 mL; HYDROGEN PEROXIDE 0.125 mL/100 mL; WATER; EUCALYPTUS OIL 0.03 mL/100 mL; PIPERONAL 0.005 mL/100 mL; LINALYL ACETATE 0.07 mL/100 mL

Lavender Hand Sanitizer 80%

The hand sanitizer is manufactured using only the following ingredients:

1. Alcohol (ethanol) (USP or Food Chemical Codex (FCC) grade) (80%, volume/volume (v/v)) in an aqueous solution denatured according to Alcohol and Tobacco Tax and Trade Bureau regulations in 27 CFR part 20.
2. Glycerol (1.45% v/v).
3. Hydrogen peroxide (0.125% v/v).
4. Sterile distilled water or boiled cold water.
5. Fragrance

Active Ingredient(s)

Alcohol 80% v/v. Purpose: Antiseptic

Purpose

Antiseptic, Hand Sanitizer

Use

Hand Sanitizer to help reduce bacteria that potentially can cause disease.

Warnings

For external use only. Flammable. Keep away from heat or flame

Do not use

- in children less than 2 months of age
- on open skin wounds

When using this product keep out of eyes, ears, and mouth. In case of contact with eyes, rinse eyes thoroughly with water.
Stop use and ask a doctor if irritation or rash occurs. These may be signs of a serious condition.
Keep out of reach of children. If swallowed, get medical help or contact a Poison Control Center right away.

Stop use and ask a doctor if irritation or rash occurs. These may be signs of a serious condition.

Keep out of reach of children. If swallowed, get medical help or contact a Poison Control Center right away.

Directions

- Place enough product on hands to cover all surfaces. Rub hands together until dry.
- Supervise children under 6 years of age when using this product to avoid swallowing.

Other information

- Store between 15-30C (59-86F)
- Avoid freezing and excessive heat above 40C (104F)

Inactive ingredients

glycerin, hydrogen peroxide, purified water USP, fragrance

Package Label - Principal Display Panel

55 gallons NDC: 75009-680-01

275 gallons NDC:75009-680-02

5 gallons NDC:75009-680-03

1 gallon NDC:75009-680-04

1 quart NDC: 75009-680-05